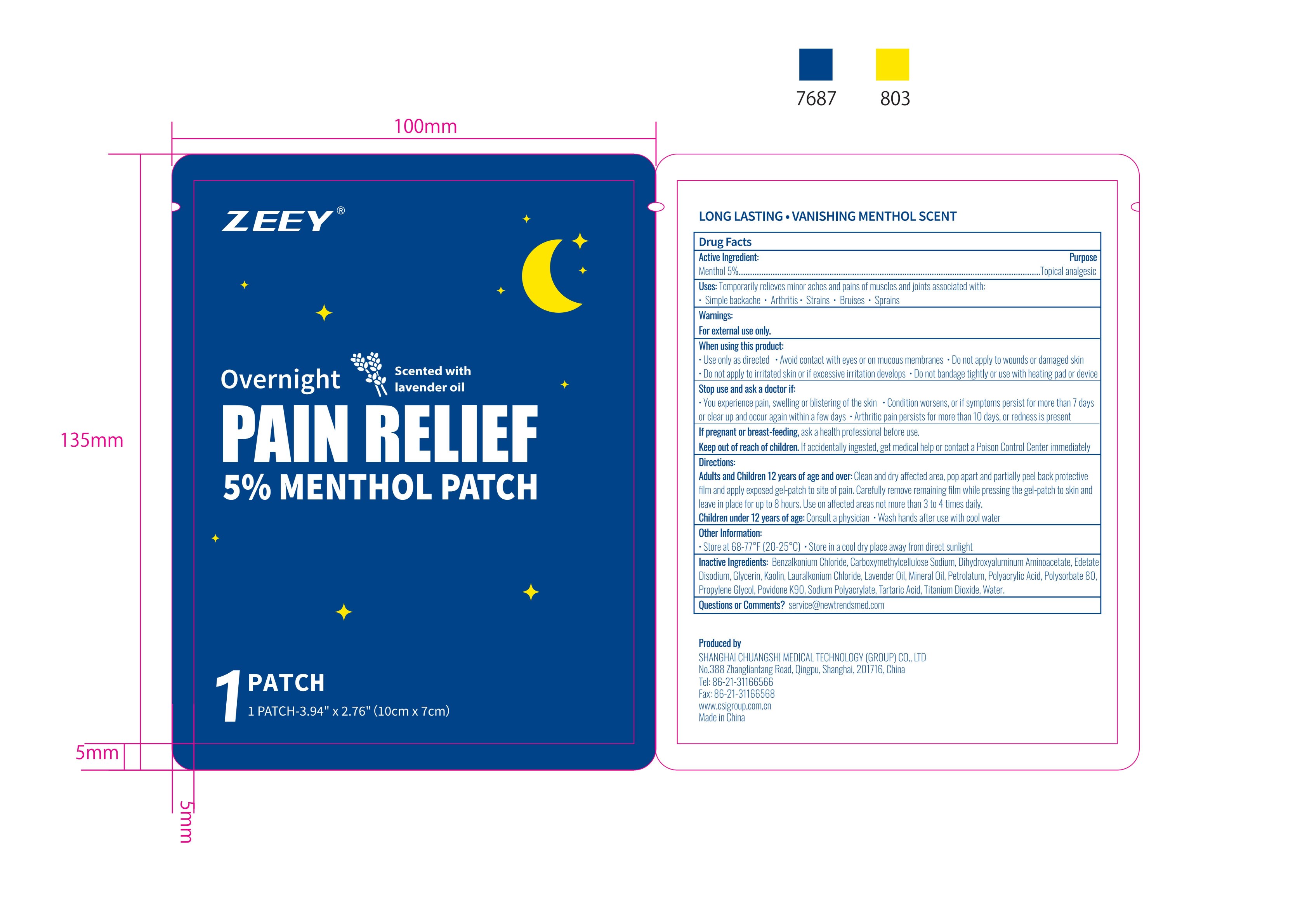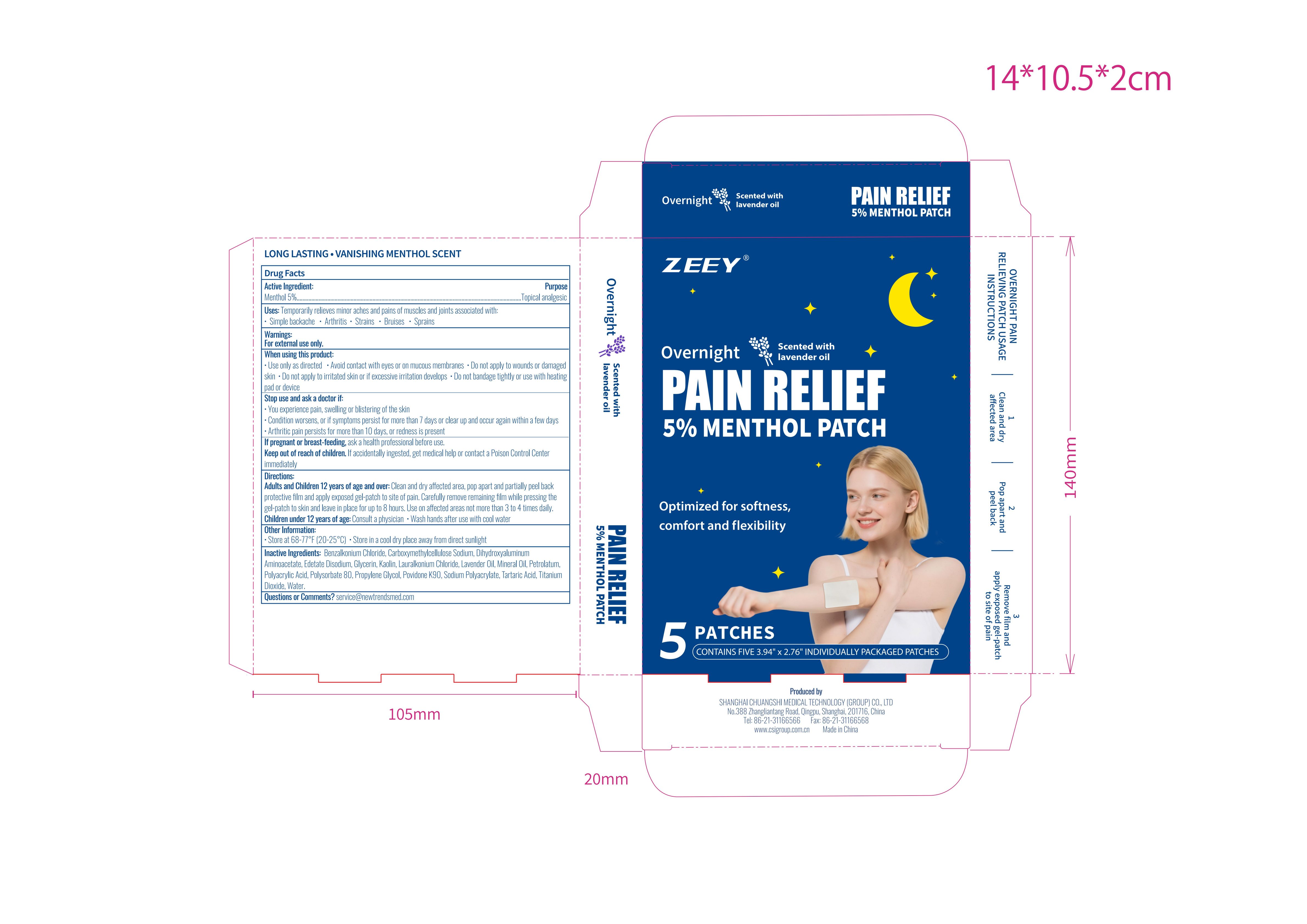 DRUG LABEL: Pain Relief
NDC: 73557-192 | Form: PATCH
Manufacturer: Shanghai Chuangshi Medical Technology (Group) Co., Ltd.
Category: otc | Type: HUMAN OTC DRUG LABEL
Date: 20250915

ACTIVE INGREDIENTS: MENTHOL 0.05 g/1 g
INACTIVE INGREDIENTS: KAOLIN; TARTARIC ACID; WATER; DIHYDROXYALUMINUM AMINOACETATE ANHYDROUS; PROPYLENE GLYCOL; POLYACRYLIC ACID (250000 MW); CARBOXYMETHYLCELLULOSE SODIUM; SODIUM POLYACRYLATE (2500000 MW); TITANIUM DIOXIDE; MINERAL OIL; PETROLATUM; BENZALKONIUM CHLORIDE; LAURALKONIUM CHLORIDE; POLYSORBATE 80; GLYCERIN; POVIDONE K90; LAVENDER OIL; EDETATE DISODIUM

73557-192

Active ingredient

Menthol 5% ...... Purpose: Topical analgesic

Purpose

Topical analgesic

Uses

Temporarily relieves minor aches and pains of muscles and joints associated with:

- simple backache
- arthrits
- strains
- bruises
- sprains

Warnings

For external use only

Ask doctor

Stop use and ask a doctor if:
• you experience pain, swelling or blistering of the skin
• condition worsens, or if symptoms persist for more than 7 days or clear up and occur again within a few days
• arthritic pain persists for more than 10 days, or redness is present

If pregnant or breastfeeding,ask a health professional before use.

When using

When using this prudocts:

• use only as directed
• avoid contact with eyes or on mucous membranes
• do not apply to wounds or damaged skin
• do not apply to irritated skin or if excessive irritation develops
• do not bandage tightly or use with heating pad or device

Do not use

• do not apply to wounds or damaged skin
• do not apply to irritated skin or if excessive irritation develops
• do not bandage tightly or use with heating pad or device

Stop use

Stop use and ask a doctor if:
• you experience pain, swelling or blistering of the skin
• condition worsens, or if symptoms persist for more than 7 days or clear up and occur again within a few days
• arthritic pain persists for more than 10 days, or redness is present

Pregnancy or breast feeding

If pregnant or breastfeeding,ask a health professional before use.

Keep out of reach of children

If accidentally ingested, get medical help or contact a Poison Control Center immediately

Directions

• adults and children 12 years of age and older: Clean and dry affected area, pop apart and partially peel back protective ﬁlm and apply exposed gel-patch to site of pain. Carefully remove remaining ﬁlm while pressing the gel-patch to skin and leave in place for up to 8 hours. Use on affected areas not more than 3 to 4 times daily.
• children under 12 years of age: consult a physician
• wash hands after use with cool water

Inactive ingredients

Benzalkonium Chloride,Carboxymethylcellulose Sodium, Dihydroxyaluminum Aminoacetate, Edetate Disodium, Glycerin,Kaolin,Lauralkonium Chloride,Lavender Oil, Mineral Oil,Petrolatum, Polyacrylic Acid,Polysorbate 80, Propylene Glycol, Povidone K90,Sodium Polyacrylate,Tartaric Acid,Titanium Dioxide,Water

Questions or comments

service@newtrendsmed.com

Other information

• store at 68-77℉ (20-25℃)

• store in a cool dry place away from direct sunlight